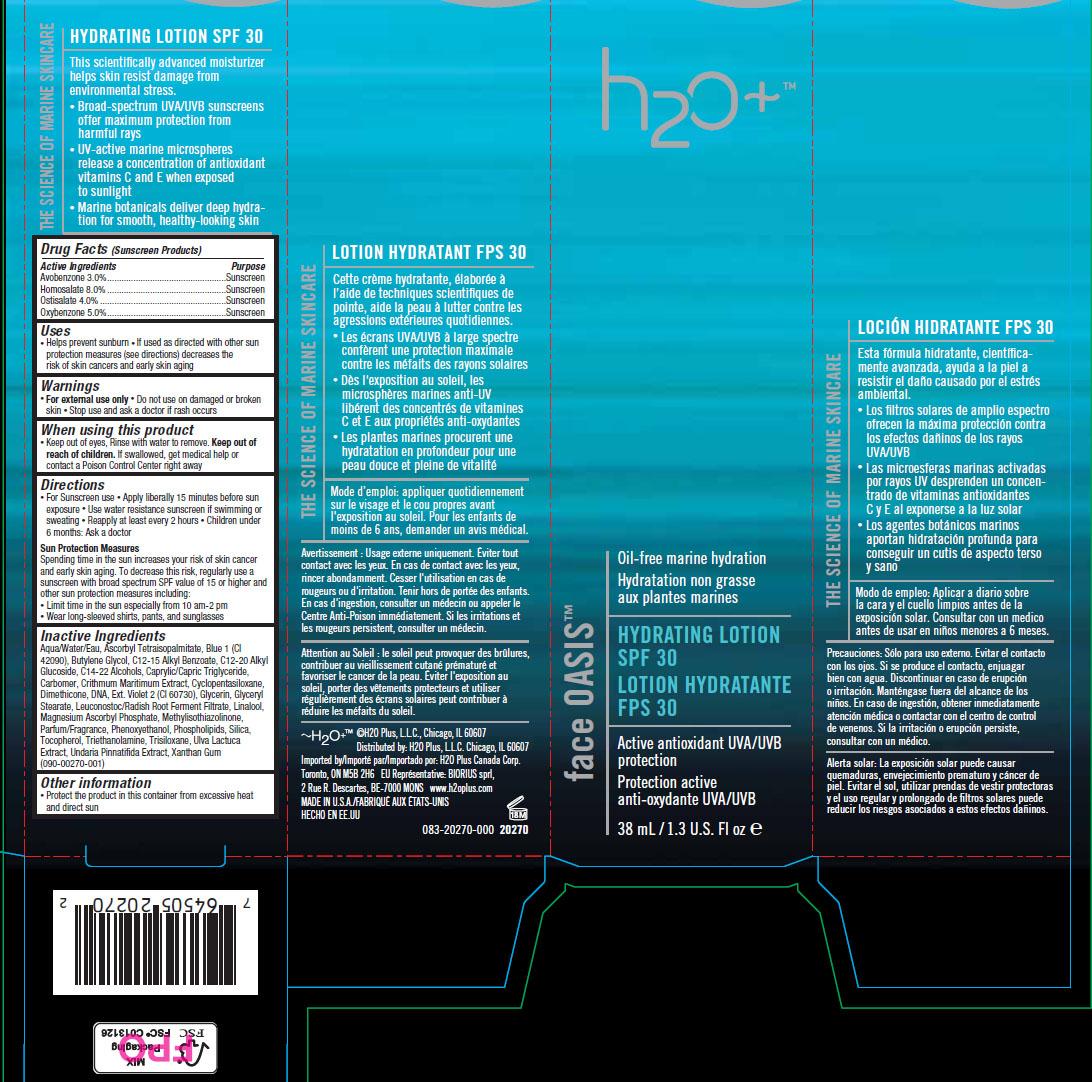 DRUG LABEL: Face Oasis Hydrating 
NDC: 65903-270 | Form: LOTION
Manufacturer: H2O PLUS
Category: otc | Type: HUMAN OTC DRUG LABEL
Date: 20110927

ACTIVE INGREDIENTS: Avobenzone 3 mL/100 mL; Homosalate 8 mL/100 mL; Octisalate 4 mL/100 mL; Oxybenzone 5 mL/100 mL
INACTIVE INGREDIENTS: water; ASCORBYL PALMITATE; BUTYLENE GLYCOL; ALKYL (C12-15) BENZOATE; C12-20 ALKYL GLUCOSIDE; MEDIUM-CHAIN TRIGLYCERIDES; CARBOMER HOMOPOLYMER TYPE C; CRITHMUM MARITIMUM; CYCLOMETHICONE 5; DIMETHICONE; HERRING SPERM DNA; GLYCERIN; GLYCERYL MONOSTEARATE; LINALOOL, (+/-)-; MAGNESIUM ASCORBYL PHOSPHATE; METHYLCHLOROISOTHIAZOLINONE; PHENOXYETHANOL; LECITHIN, SOYBEAN; SILICON DIOXIDE; TOCOPHEROL; TRIETHANOLAMINE HYDROCHLORIDE; TRISILOXANE; ULVA LACTUCA; UNDARIA PINNATIFIDA; XANTHAN GUM

Drug Facts

ACTIVE INGREDIENT

Avobenzone 3.0%
Homosalate 8.0%
Octisalate 4.0%
Oxybenzone 5.0%

PURPOSE

Sunscreen
Sunscreen
Sunscreen
Sunscreen

WHEN USING

Helps prevent sunburn
If used as directed with other sun protection measures
(see directions) decreases the risk of skin cancers and early skin aging

WARNINGS

For external use only • Do not use on damaged or broken skin
• Stop use and ask a doctor if rash occurs

Keep out of eyes, Rinse with water to remove. Keep out of reach of children.
If swallowed, get medical help or contact a Poison Control Center right away

DOSAGE AND ADMINISTRATION

• For Sunscreen use
• Apply liberally 15 minutes before sun exposure
• Use water resistance sunscreen if swimming or sweating
• Reapply at least every 2 hours
• Children under 6 months: Ask a doctor

STORAGE AND HANDLING

Protect the product in this container from excessive heat
and direct sun

INACTIVE INGREDIENT

Aqua/Water/Eau, Ascorbyl Tetraisopalmitate, Blue 1 (CI 42090), Butylene
Glycol, C12-15 Alkyl Benzoate, C12-20 Alkyl Glucoside, C14-22 Alcohols,
Caprylic/Capric Triglyceride, Carbomer, Crithmum Maritimum Extract,
Cyclopentasiloxane, Dimethicone, DNA, Ext. Violet 2 (CI 60730), Glycerin,
Glyceryl Stearate, Leuconostoc/Radish Root Ferment Filtrate, Linalool,
Magnesium Ascorbyl Phosphate, Methylisothiazolinone,
Parfum/Fragrance, Phenoxyethanol, Phospholipids, Silica, Tocopherol,
Triethanolamine, Trisiloxane, Ulva Lactuca Extract, Undaria Pinnatifida
Extract, Xanthan Gum

Image of Carton Label fa270.jpg